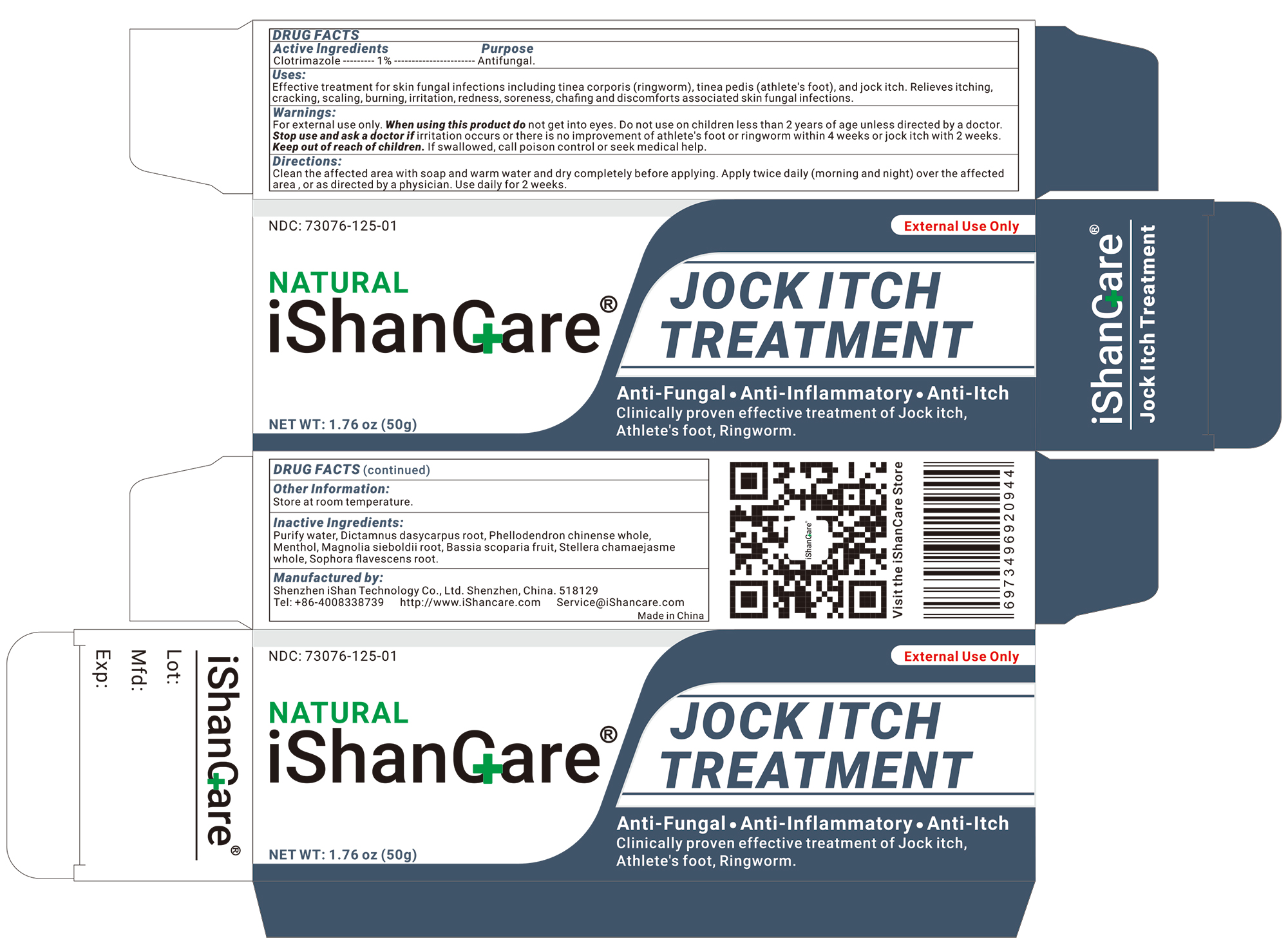 DRUG LABEL: iShanCare Jock Itch Treatment
NDC: 73076-157 | Form: CREAM
Manufacturer: Shenzhen Ishan Technology Co., Ltd
Category: homeopathic | Type: HUMAN OTC DRUG LABEL
Date: 20260213

ACTIVE INGREDIENTS: OATMEAL 1 g/100 g
INACTIVE INGREDIENTS: MAGNOLIA SIEBOLDII ROOT 3 g/100 g; STELLERA CHAMAEJASME WHOLE 3 g/100 g; SOPHORA FLAVESCENS ROOT 3 g/100 g; MENTHOL 1 g/100 g; DICTAMNUS DASYCARPUS ROOT 3 g/100 g; PHELLODENDRON CHINENSE WHOLE 3 g/100 g; BASSIA SCOPARIA FRUIT 3 g/100 g; WATER

Active ingredients

Clotrimazole----1%----Antifungal

Inactive ingredients

Purify water, dictamnus dasycarpus root, phellodendron chinense whole, Menthol. Magnolia Sieboldii Root, bassia scoparia fruit, stellera chamaejasme whole, sophora flavescens root.

Keep out of reach of children

if swallowed, call poison control or seek medical help.

ask a doctor if

irritation occurs or there is no improvement of athlete's foot or ringworm within 4 weeks or jock itch with 2 weeks

Stop use

on children less than 2 years of age unless directed by a doctor

USES

Effective treatment for skin fungal infections including tinea corporis (ringworm), tinea pedis (athlete's foot), and jock itch.
Relieves itching, cracking, scaling, burning, irritation, redness, soreness, chafing and discomforts associated skin fungal infections.

Other information

Store at room temperature.

Dosage & admimistration

Apply as needed

When using this product

do not get into eyes

Warning

For external use only

Indication & usage section

Apply as needed